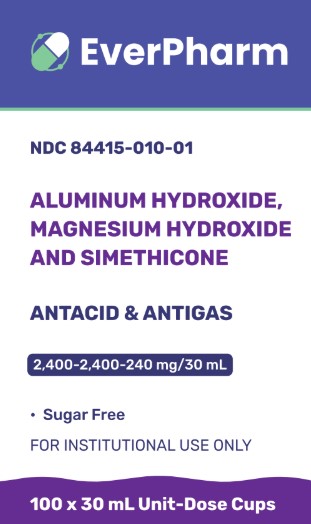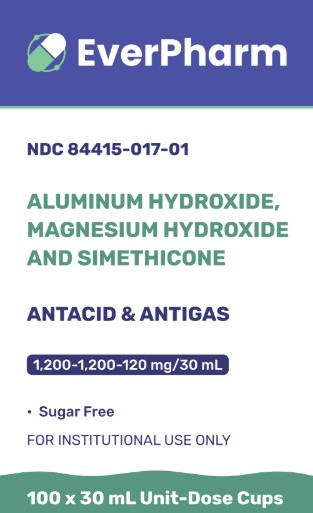 DRUG LABEL: Aluminum Hydroxide, Magnesium Hydroxide and Simethicone
NDC: 84415-017 | Form: SUSPENSION
Manufacturer: Everpharm LLC
Category: otc | Type: HUMAN OTC DRUG LABEL
Date: 20250116

ACTIVE INGREDIENTS: ALUMINUM HYDROXIDE 1200 mg/30 mL; MAGNESIUM HYDROXIDE 1200 mg/30 mL; DIMETHICONE 120 mg/30 mL
INACTIVE INGREDIENTS: BENZYL ALCOHOL; BUTYLPARABEN; CARBOXYMETHYLCELLULOSE SODIUM; HYPROMELLOSE, UNSPECIFIED; MICROCRYSTALLINE CELLULOSE; PROPYLPARABEN; WATER; SACCHARIN SODIUM; SORBITOL SOLUTION

Aluminum Hydroxide, Magnesium Hydroxide and Simethicone 1,200-1,200-120 mg/30 mL
Aluminum Hydroxide, Magnesium Hydroxide and Simethicone 2,400-2,400-240 mg/30 mL

Drug Facts

ACTIVE INGREDIENT

PURPOSE

1,200-1,200-120 mg/30 mL

Active ingredient per 30mL (1 Unit Dose)
Aluminum hydroxide 1,200mg (equivalent to dried gel USP)
Magnesium hydroxide 1,200mg
Simethicone 120mg

2,400-2,400-240 mg/30 mL

Active ingredient per 30mL (1 Unit Dose)
Aluminum hydroxide 2,400mg (equivalent to dried gel USP)
Magnesium hydroxide 2,400mg
Simethicone 240mg

Purpose

Antacid

Antigas

Uses

relieves

• heartburn

• sour stomach

• acid indigestion

• the symptoms referred to as gas

Warnings

Ask a doctor before use if you have

• kidney disease

• a magnesium restricted diet

Ask a doctor or pharmacist before use if you aretaking a prescription drug. Antacids may interact with certain prescription drugs

Stop use and ask a doctor ifsymptoms last more than 2 weeks

PREGNANCY OR BREAST FEEDING

If pregnant or breast-feeding,ask a healthcare professional before use

Keep out of reach of children.In case of accidental overdose, get medical help or contact a Poison Control Center right away (1-800-222-1222)

Directions • shake well before use

1,200-1,200-120 mg/30 mL

• Do not use more than 4 unit dose (120 mL) in a 24 hour period or use the maximum dose for more than 2 weeks

age | dose
Adults and children over 12 years of age | Take 30 mL, one unit dose, between meals and at bedtime, or as directed by a doctor. Do not exceed 4 x 30 mL unit dose (120 mL) in a 24 hour period
Children under 12 years of age | Ask a doctor

2,400-2,400-240 mg/30 mL

• Do not use more than 2 unit dose (60 mL) in a 24 hour period or use the maximum dose for more than 2 weeks

age | dose
Adults and children over 12 years of age | Take 30 mL, one unit dose, one to two times daily or as directed by a doctor. Do not exceed 2 x 30 mL unit dose (60 mL) in a 24 hour period
Children under 12 years of age | Ask a doctor

Other information

1,200-1,200-120 mg/30 mL

• each 30 mL (unit dose) containsmagnesium 510 mg and sodium 18 mg

• store at 20° to 25°C (68° to 77°F). [See USP Controlled Room Temperature]

• protect from freezing

• do not use if lid is torn or broke

2,400-2,400-240 mg/30 mL

• each 30 mL (unit dose) containsmagnesium 990 mg and sodium 6 mg

• store at 20° to 25°C (68° to 77°F). [See USP Controlled Room Temperature]

• protect from freezing

• do not use if lid is torn or broken

INACTIVE INGREDIENT

Inactive ingredientsbenzyl alcohol, butylparaben, carboxy-methycellulose sodium, flavor, hypromellose, microcrystalline cellulose, propylparaben, purified water, saccharin sodium, sorbitol solution

Questions or comments?Call (866) 838-3774

PACKAGE LABEL.PRINCIPAL DISPLAY PANEL

EverPharm

NDC 84415-017-01

Aluminum Hydroxide
Magnesium Hydroxide
and Simethicone

Antacid & Antigas

1,200-1,200-120 mg/30 mL

• Sugar Free

For Institutional Use Only

100 x 30 mL Unit-Dose Cups

PACKAGE LABEL.PRINCIPAL DISPLAY PANEL

EverPharm

NDC 84415-010-01

Aluminum Hydroxide
Magnesium Hydroxide
and Simethicone

Antacid & Antigas

2,400-2,400-240 mg/30 mL

• Sugar Free

For Institutional Use Only

100 x 30 mL Unit-Dose Cups